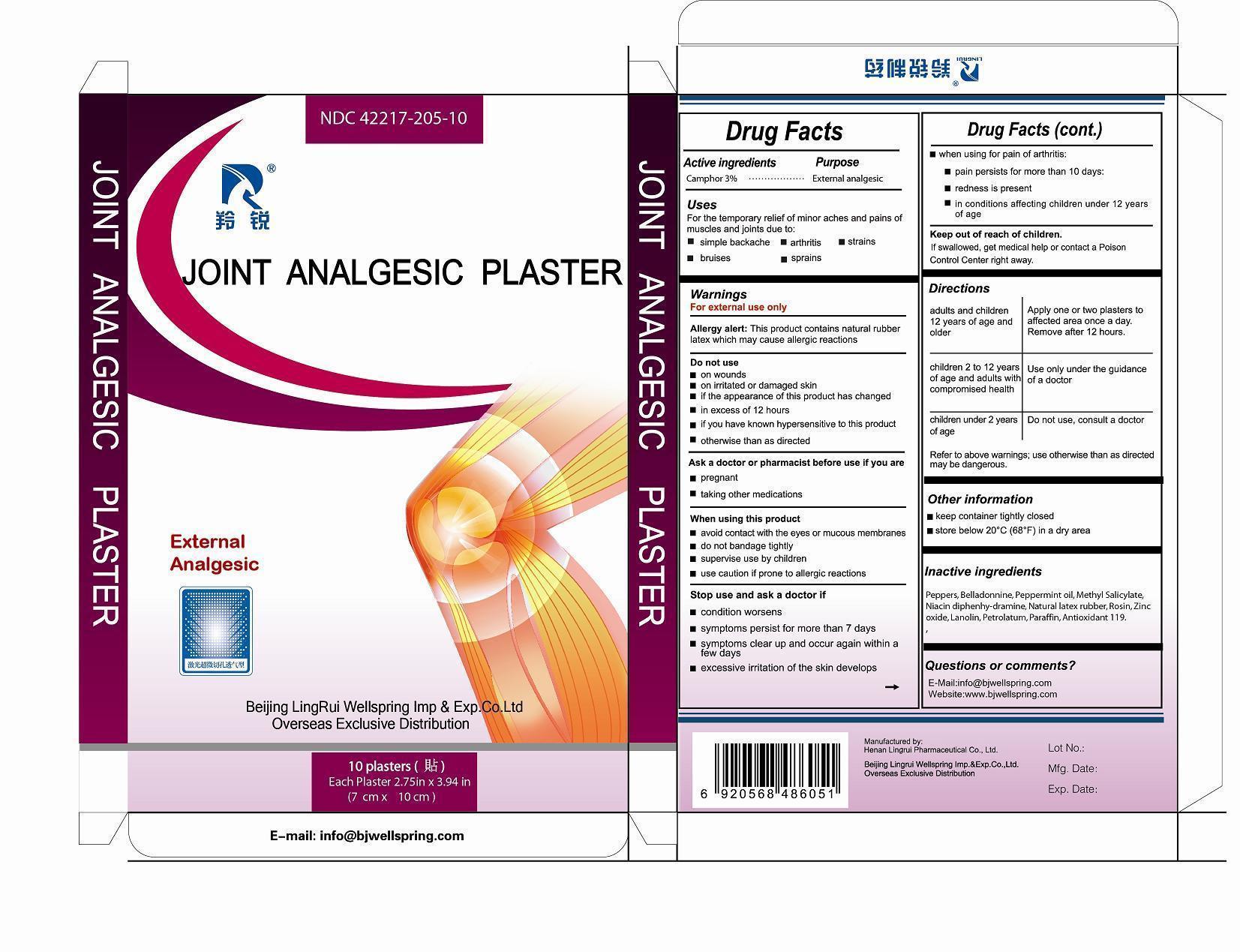 DRUG LABEL: Joint Analgesic Plaster
NDC: 42217-205 | Form: PLASTER
Manufacturer: Henan Lingrui Pharmaceutical Co Ltd
Category: otc | Type: HUMAN OTC DRUG LABEL
Date: 20150313

ACTIVE INGREDIENTS: CAMPHOR (SYNTHETIC) 3 g/100 g
INACTIVE INGREDIENTS: PEPPERS; BELLADONNINE; PEPPERMINT OIL; METHYL SALICYLATE; NIACIN; DIPHENHYDRAMINE; ROSIN; NATURAL LATEX RUBBER; ZINC OXIDE; LANOLIN; PETROLATUM; PARAFFIN; ANTIOXIDANT 119

Henan Lingrui Pharmaceutical Co Ltd

ACTIVE INGREDIENTS

Camphor 3%

PURPOSE

Camphor External Analgesic

USES

For the temporary relief of minor aches and pains of muscles and joints due to:

simple backache

arthritis

strains

bruises

sprains

WARNINGS

For External Use only.

Allergy Alert: This product contains natural rubber latex which may cause allergic reactions.

DO NOT USE

on wounds

on irritated or damaged skin

if the appearance of this product has changed

in excess of 12 hours

if you have known hypersensitive to this product

otherwise than as directed

ASK A DOCTOR OR PHARMACIST BEFORE USE IF YOU ARE

pregnant

taking other medications

WHEN USING THIS PRODUCT

avoid contact with the eye or mucous membranes

do not bandage tightly

supervise use by children

use caution if prone to allergic reactions

STOP USE AND ASK A DOCTOR IF

condition worsens

symptoms persist for more than 7 days

symptoms clear up and occur again within a few days

excessive irritation of the skin develops

when using for pain of arthritis

pain persists for more than 10 days

redness is present

in conditions affecting children under 12 years of age

KEEP OUT OF REACH OF CHILDREN.

If swallowed, get medical help or contact a Poison Control Center right away.

DIRECTIONS

Adults and children 12 years of age and older: Apply one or two plasters to affected area once a day. Remove after 12 hours.
Children 2 to 12 years of age and adults with compromised health: Use only under the guidance of a doctor.
Children under 2 years of age: Do not use, consult a doctor.
Refer to the above warnings: use otherwise than as directed may be dangerous.

OTHER INFORMATION

Keep container tightly closed.

Store below 20 ℃ (68 ℉) in a dry area.

INACTIVE INGREDIENTS

PEPPERS, BELLADONNINE, PEPPERMINT OIL, METHYL SALICYLATE, NIACIN, DIPHENHYDRAMINE, NATURAL LATEX RUBBER, ROSIN, ZINC OXIDE, LANOLIN, PETROLATUM, PARAFFIN, ANTIOXIDANT 119

QUESTIONS OR COMMENTS?

E-mail: info@bjwellspring.com

Website: www.bjwellspring.com

Manufactured by

Henan Lingrui Pharmaceutical Co.; Ltd.

232 Xiang Yang Road, Xin County, Henan, China

Beijing Lingrui Wellspring Imp. & Exp. Co.; Ltd.

Overseas Exclusive Distribution